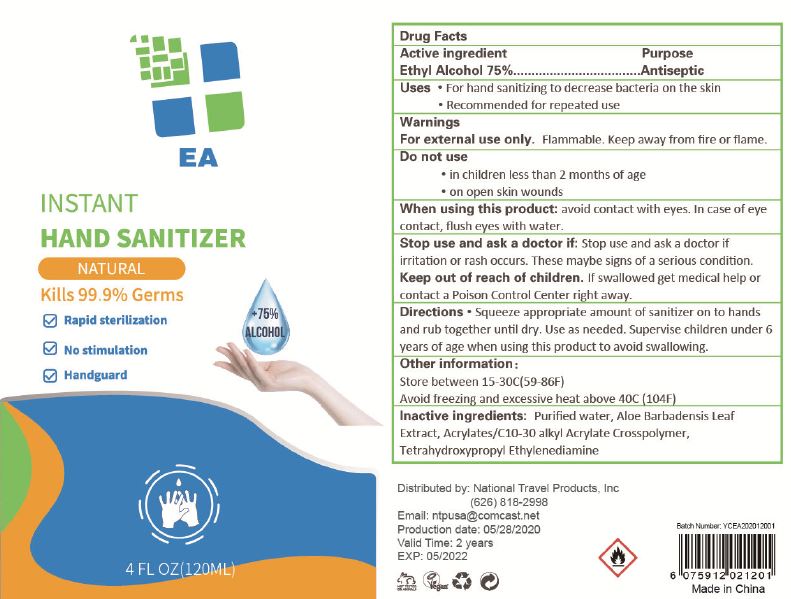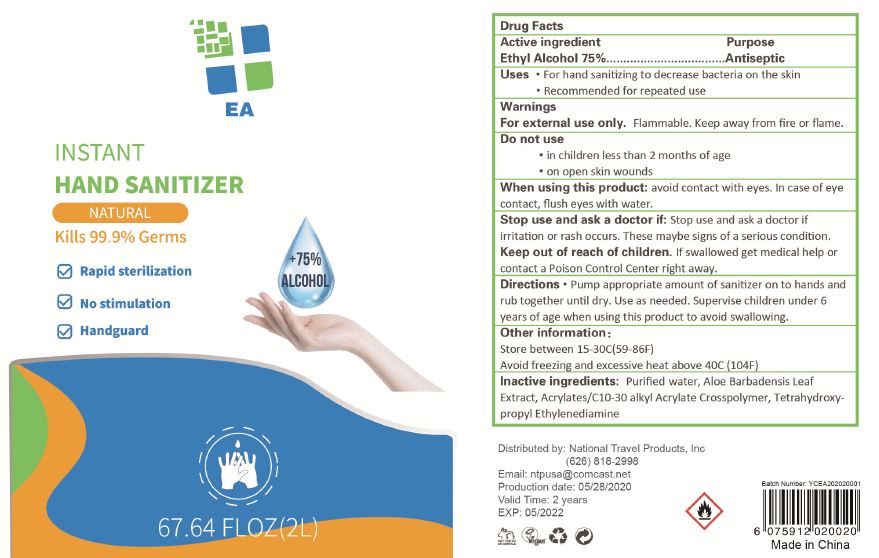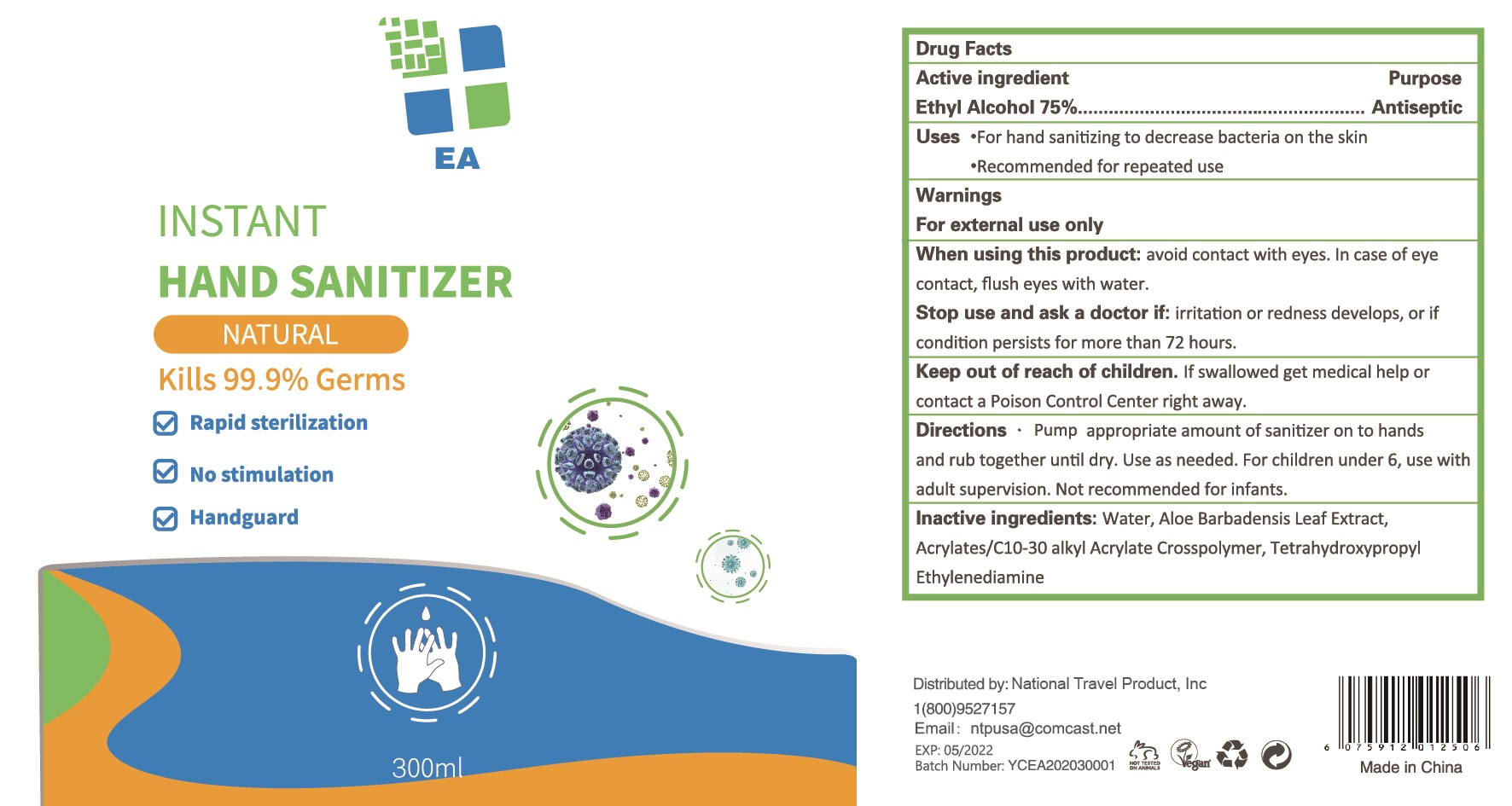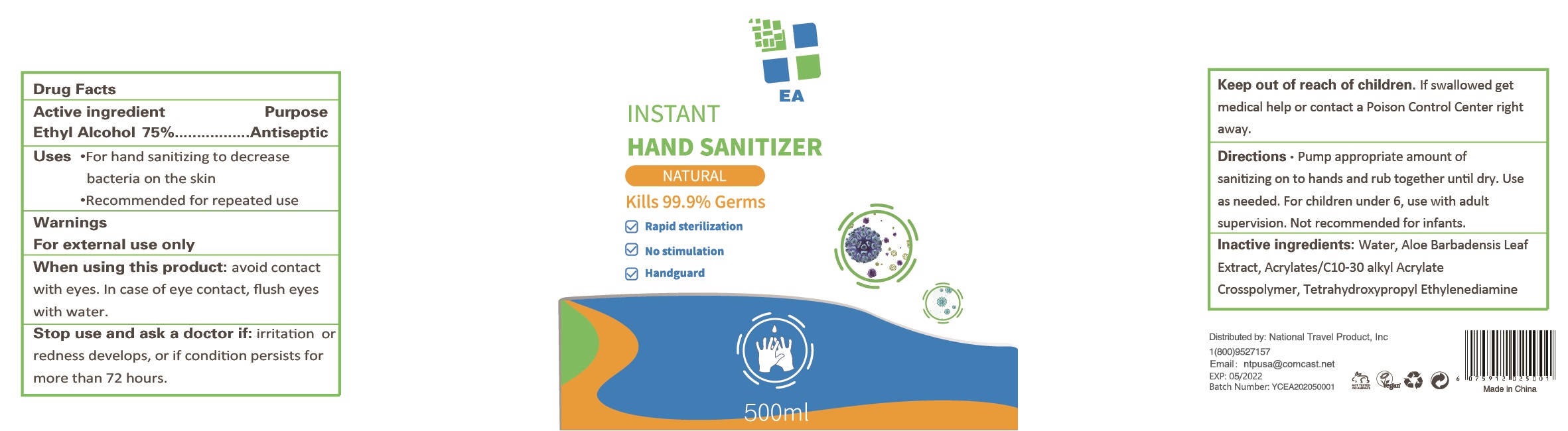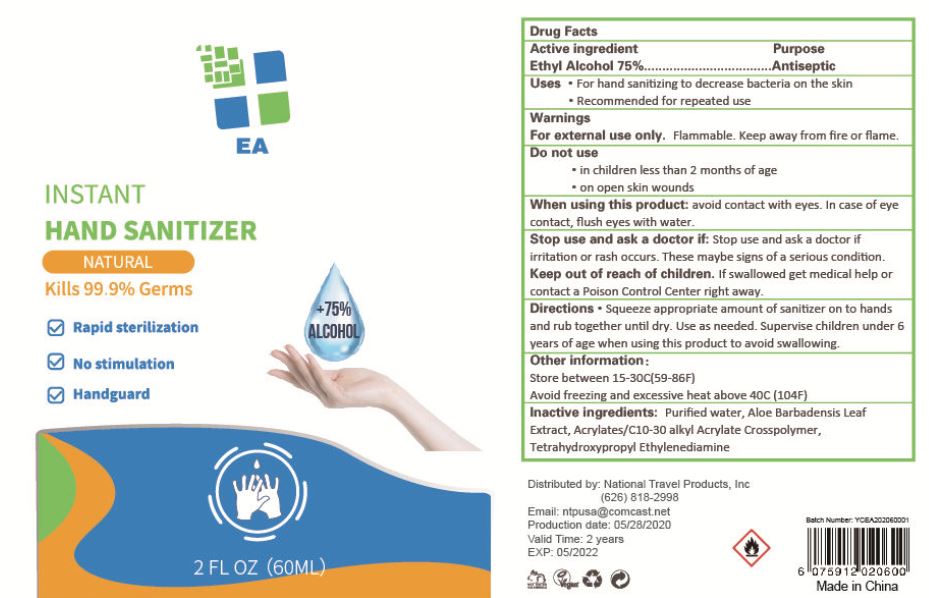 DRUG LABEL: EA INSTANT HAND SANITIZER
NDC: 78233-013 | Form: GEL
Manufacturer: National Travel Product, Inc
Category: otc | Type: HUMAN OTC DRUG LABEL
Date: 20200611

ACTIVE INGREDIENTS: ALCOHOL 0.75 1/1 mL
INACTIVE INGREDIENTS: WATER; ALOE VERA LEAF; CARBOMER INTERPOLYMER TYPE A (ALLYL SUCROSE CROSSLINKED); EDETOL

EA INSTANT HAND SANITIZER

Active ingredient

Ethyl Alcohol 75%

Purpose

Antiseptic

Uses

- For hand sanitizing to decrease bacteria on the skin
- Recommended for repeated use

Warnings

For external use only

When using this product:

avoid contact with eyes. In case of eye contact, flush eyes with water.

Stop use and ask a doctor if:

irritation or redness develops, or if condition persists for more than 72 hours.

Keep out of reach of children.

If swallowed get medical help or contact a Poison Control Center right away.

Directions

- Pump appropriate amount of sanitizer on to hands and rub together until dry. Use as needed. For children under 6, use with adult supervison. Not recommended for infants.

Inactive ingredients:

Water, Aloe Barbadensis Leaf Extract, Acrylates/C10-30 alkyl Acrylate Crosspolymer, Tetrahydroxypropyl Ethylenediamine.